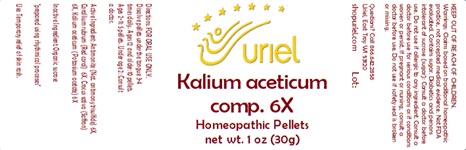 DRUG LABEL: Kalium aceticum comp 6
NDC: 48951-6079 | Form: PELLET
Manufacturer: Uriel Pharmacy Inc.
Category: homeopathic | Type: HUMAN OTC DRUG LABEL
Date: 20240112

ACTIVE INGREDIENTS: SAFFRON 6 [hp_X]/1 1; POTASSIUM ACETATE 6 [hp_X]/1 1; ANTIMONY TRISULFIDE 6 [hp_X]/1 1; CORALLIUM RUBRUM EXOSKELETON 6 [hp_X]/1 1
INACTIVE INGREDIENTS: SUCROSE

Kalium aceticum comp 6X

INDICATIONS AND USAGE

Directions: FOR ORAL USE ONLY.

DOSAGE AND ADMINISTRATION

Dissolve pellets under the tongue 3-4 times daily. Ages 12 and older: 10 pellets. Ages 2-11: 5 pellets. Under age 2: Consult
a doctor.

Active Ingredient: Antimonite (Nat. antimony trisulfide) 6X, Corallium rubrum (Red coral) 6X, Crocus sativa (Saffron) 6X, Kalium aceticum (Potassium acetate) 6X

Inactive Ingredient: Organic sucrose

"prepared using rhythmical processes"

PURPOSE

Use: Temporary relief of skin rash.

KEEP OUT OF REACH OF CHILDREN.

WARNINGS

Warnings: Claims based on traditional homeopathic practice, not accepted medical evidence. Not FDA evaluated. Contains sugar. Diabetics and persons intolerant of sucrose (sugar): Consult a doctor before use. Contains traces of lactose. Do not use if allergic to any ingredient. Consult a doctor before use for serious conditions or if conditions worsen or persist. If pregnant or nursing,
consult a doctor before use. Do not use if safety seal is broken or missing.

Questions? Call 866.642.2858
Uriel, East Troy, WI 53120
shopuriel.com Lot: